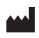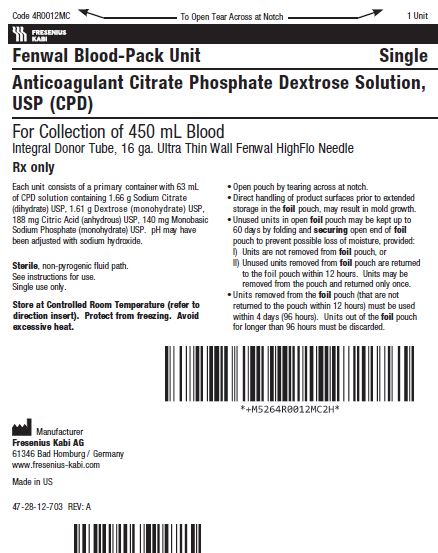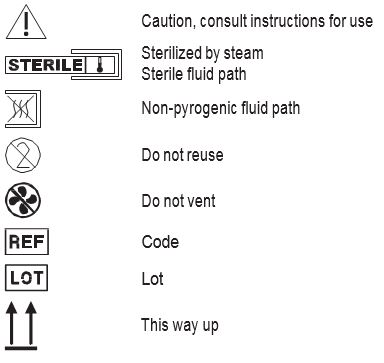 DRUG LABEL: Anticoagulant Citrate Phosphate Dextrose (CPD) Blood-Pack Units in PL 146 Plastic
NDC: 0942-9202 | Form: SOLUTION
Manufacturer: Fenwal, Inc.
Category: prescription | Type: HUMAN PRESCRIPTION DRUG LABEL
Date: 20221101

ACTIVE INGREDIENTS: TRISODIUM CITRATE DIHYDRATE 1.66 g/63 mL; DEXTROSE MONOHYDRATE 1.61 g/63 mL; ANHYDROUS CITRIC ACID 188 mg/63 mL; SODIUM PHOSPHATE, MONOBASIC, MONOHYDRATE 140 mg/63 mL
INACTIVE INGREDIENTS: SODIUM HYDROXIDE

Anticoagulant Citrate Phosphate Dextrose Solution, USP (CPD) BLOOD-PACK™ Unit

4R0012MC, 4R0837MC, 4R0112MC
Fenwal Blood-Pack Units
Rx only
With Integral Donor Tube Using ACD or CPD and Fenwal HighFlo Needle
Instructions for Use
Collection Procedure:
Use aseptic technique.
Precaution: Do not use unless solution is clear.
1. Identify Blood-Pack unit using appropriate donor identification system. Confirm that all numbered tubing of each Blood-Pack unit contains its own identical segment numbers.
2. Adjust donor scale to desired collection weight.
3. Position primary container from donor scale as far as possible below donor arm and clamp donor tubing.
4. Following blood center procedures, apply pressure to donor's arm and disinfect site of venipuncture.
5. Remove HighFlo^1 needle cover per instructions below:
a) Holding the hub and cover near the tamper-evident seal, twist cover and hub in opposite directions to break seal.
b) Remove needle cover, being careful not to drag the cover across the needle point.
Following blood center procedures, perform venipuncture, appropriately secure donor needle and/or tubing and release clamp.
6. Mix blood and anticoagulant at several intervals during collection and immediately after collection.
7. Collect the appropriate volume based on Blood-Pack unit used.
Note: The volume of anticoagulant is sufficient for the blood collection indicated on Blood-Pack unit ± 10%.
8. Apply clamp to donor tube.
9. As appropriate, release pressure on the donor's arm, collect donor samples following established procedures and withdraw donor needle.
10. Withdrawal of needle into needle guard.
Precaution: The needle guard must be held stationary while the needle is withdrawn into it.
a) Hold sides of needle guard near the front, between the index finger and thumb. Pull the hub back smoothly until the needle is completely enclosed and securely locked into the needle guard.
b) Confirm the needle is completely enclosed and securely locked into the needle guard.
11. Strip blood from donor tubing into container, mix and allow the tubing to refill; repeat once. Seal at X marks on donor tubing to provide numbered aliquots of anticoagulated blood for typing or crossmatching.
12. Discard needle in needle guard into an appropriate biohazardous waste container following established procedures.
13. Store filled unit between 1 and 6° C.
14. Infuse blood within 21 days of collection.
Store at Controlled Room Temperature. Protect from freezing. Avoid excessive heat.
Definition of "Controlled Room Temperature":
"A temperature maintained thermostatically that encompasses the usual and customary working environment of 20° to 25°C (68° to 77°F); that results in a mean kinetic temperature calculated to be not more than 25°C; and that allows for excursions between 15°C and 30°C (59° and 86°F) that are experienced in pharmacies, hospitals, and warehouses. Provided the mean kinetic temperature remains in the allowed range, transient spikes up to 40°C are permitted as long as they do not exceed 24 hours ... The mean kinetic temperature is a calculated value that may be used as an isothermal storage temperature that simulates the non isothermal effects of storage temperature variations."
Reference: United States Pharmacopeia, General Notices. United States Pharmacopeial Convention, Inc.
12601 Twinbrook Parkway, Rockville, MD.
Symbols with Definitions
^1 Van der Meer, P.F., & de Korte, D. "Increase of blood donation speed by optimizing the needle-to-tubing connection: an application of donation software." Vox Sanguinis 2009, 97: 21-25

Manufacturer
Fresenius Kabi AG
61346 Bad Homburg / Germany
www.fresenius-kabi.com
1-800-933-6925
© 2019 Fresenius Kabi AG. All rights reserved.
47-23-13-621 REV: A

PACKAGE/LABEL DISPLAY PANEL

Code 4R0012MC

1 Unit
Fresenius Kabi

Fenwal Blood-Pack Unit
Single

Anticoagulant Citrate Phosphate Dextrose Solution, USP (CPD)
For Collection of 450 mL Blood
Integral Donor Tube, 16 ga. Ultra Thin Wall Fenwal HighFlo Needle

Rx only

Each unit consists of a primary container with 63 mL of CPD solution containing 1.66 g Sodium Citrate (dihydrate) USP, 1.61 g Dextrose (monohydrate) USP, 188 mg Citric Acid (anhydrous) USP, 140 mg Monobasic Sodium Phosphate (monohydrate) USP. pH may have been adjusted with sodium hydroxide.

Sterile, non-pyrogenic fluid path.
See instructions for use.
Single Use Only

Store at Controlled Room Temperature (refer to direction insert). Protect from freezing. Avoid excessive heat.

- Open pouch by tearing across at notch.
- Direct handling of product surfaces prior to extended storage in the foil pouch, may result in mold growth.
- Unused units in open foil pouch may be kept up to 60 days by folding and securing open end of foil pouch to prevent possible loss of moisture, provided:
- Units are not removed from foil pouch, or
- Unused units removed from foil pouch are returned to the foil pouch within 12 hours. Units may be removed from the pouch and returned only once.
- Units removed from the foil pouch (that are not returned to the pouch within 12 hours) must be used within 4 days (96 hours). Units out of the foil pouch for longer than 96 hours must be discarded.

Manufacturer
Fresenius Kabi AG
61346 Bad Homburg / Germany
www.fresenius-kabi.com
Made in US
47-28-12-703 REV: A